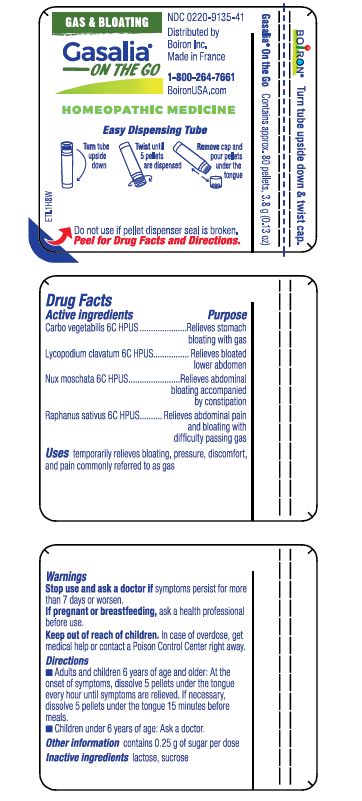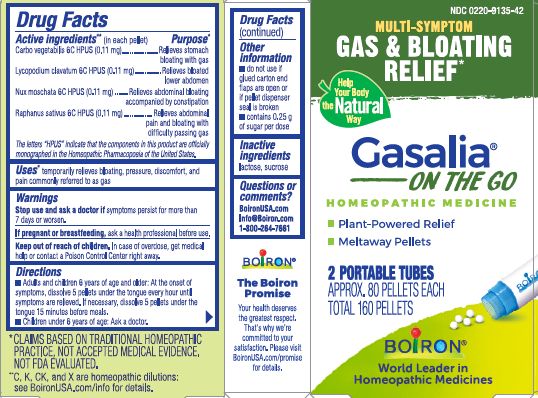 DRUG LABEL: GASALIA
NDC: 0220-9135 | Form: PELLET
Manufacturer: Boiron
Category: homeopathic | Type: HUMAN OTC DRUG LABEL
Date: 20231004

ACTIVE INGREDIENTS: RADISH 6 [hp_C]/1 1; LYCOPODIUM CLAVATUM SPORE 6 [hp_C]/1 1; ACTIVATED CHARCOAL 6 [hp_C]/1 1; NUTMEG 6 [hp_C]/1 1
INACTIVE INGREDIENTS: LACTOSE, UNSPECIFIED FORM; SUCROSE

Gasalia Pellets

Active ingredients** (in each pellet)

Carbo vegetabilis 6C HPUS (0.11 mg)

Lycopodium clavatum 6C HPUS (0.11 mg)

Nux Moschata 6C HPUS (0.11 mg)

Raphanus sativus 6C HPUS (0.11 mg)

The letters "HPUS" indicate that the components in this product are officially monographed in the Homeopathic Pharmacopoeia of the United States.

Purpose*

Carbo Vegetabilis 6C HPUS (0.11 mg) ... Relieves stomach bloating with gas

Lycopodium clavatum 6C HPUS (0.11 mg) ... Relieves bloated lower abdomen

Nux moschata 6C HPUS (0.11 mg) ... Relieves abdominal bloating accompanied by constipation

Raphanus sativus 6C HPUS (0.11 mg) ... Relieves abdominal pain and bloating with difficulty passing gas

Uses*

temporarily relieves bloating, pressure, discomfort, and pain commonly referred to as gas

Stop use and ask a doctor if symptoms persist for more than 7 days or worsen.

PREGNANCY OR BREAST FEEDING

If pregnant or breastfeeding, ask a health professional before use.

Keep out of reach of children. In case of overdose, get medical help or contact a Poison Control Center right away.

DOSAGE AND ADMINISTRATION

- Adults and children 6 years of age and older: At the onset of symptoms, dissolve 5 pellets under the tongue every hour until symptoms are relieved. If necessary, dissolve 5 pellets under the tongue 15 minutes before meals.
- Children under 6 years of age: Ask a doctor.

INACTIVE INGREDIENT

lactose, sucrose

- do not use if glue carton end flaps are open if pellet dispenser seal is broken
- contains 0.25 g of sugar per pose

Multi-Symptom

Gas & Bloating Relief*

Plant-Powered Relief

Meltaway Pellets

2 PORTABLE TUBES

APPROX. 80 PELLETS EACH

TOTAL 160 PELLETS

Contains approx. 80 pellets, 3.8 g (0.13 oz)

Turn tube upside down

Twist until 5 pellets are dispensed

Remove cap and pour pellets under the tongue

Do not use if pellet dispenser seal is broken.

*CLAIMS BASED ON TRADITIONAL HOMEOPATHIC PRACTICE NOT ACCEPTED MEDICAL EVIDENCE. NOT FDA EVALUATED.
**C,K,CK, and X are homeopathic dilutions: see BoironUSA.com/info for details.

QUESTIONS

BoironUSA.com

Info@Boiron.com

1-800-264-7661

Made in France

Distributed by

Boiron, Inc.

Newtown Square, PA

19073